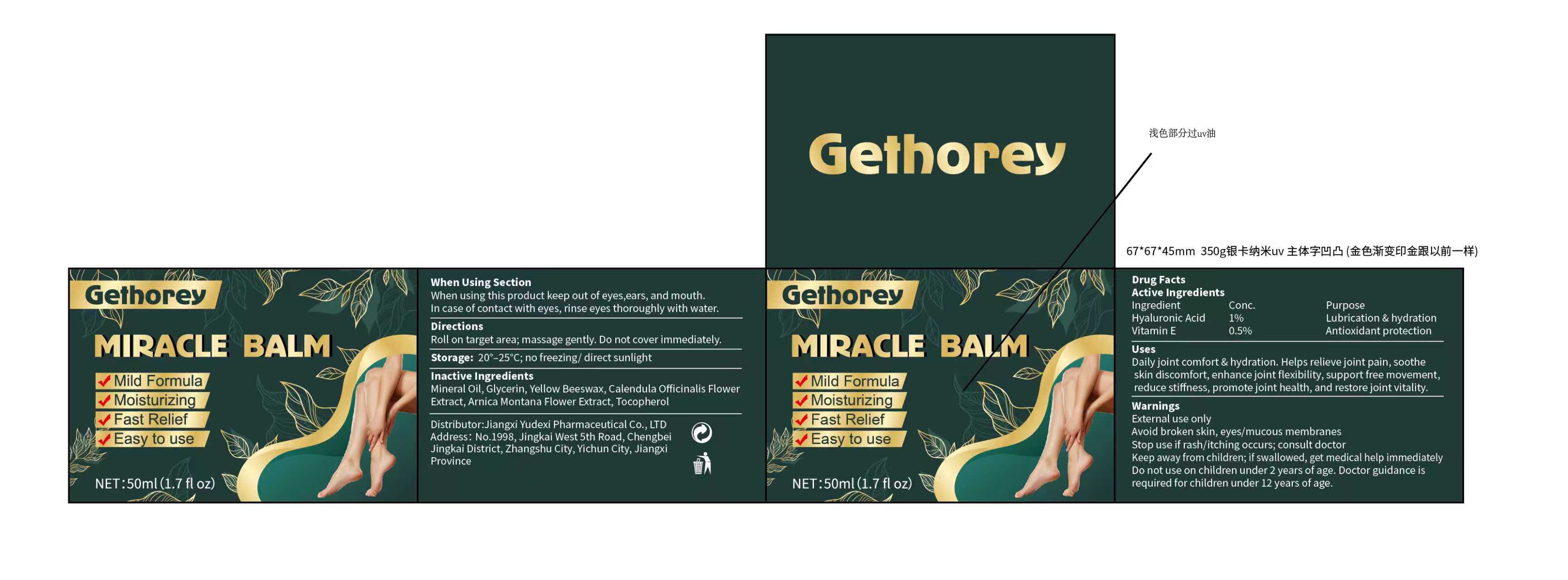 DRUG LABEL: Gethorey MIRACLE BALM
NDC: 85248-013 | Form: CREAM
Manufacturer: Jiangxi Yudexi Pharmaceutical Co., LTD
Category: otc | Type: HUMAN OTC DRUG LABEL
Date: 20260127

ACTIVE INGREDIENTS: .ALPHA.-TOCOPHEROL 0.5 g/100 mL; HYALURONIC ACID 1 g/100 mL
INACTIVE INGREDIENTS: YELLOW WAX; CALENDULA OFFICINALIS FLOWER; MINERAL OIL; GLYCERIN; TOCOPHEROL; ARNICA MONTANA FLOWER

85248-013

Active Ingredient

Hyaluronic Acid1 % Vitamin E 0.5%

Purpose

Lubrication & hydration Antioxidant protection

Use

Daily joint comfort & hydration. Helps relieve joint pain, soothe skin discomfort, enhance joint flexibility, support free movement,reduce stiffness, promote joint health, and restore joint vitality.

Warnings

External use only,Avoid broken skin, eyes/mucous membranes

Do not use on children under 2 years of age. Doctor guidance is required for children under 12 years of age.

When Using

When using this product keep out of eyes,ears, and mouth.In case of contact with eyes, rinse eyes thoroughly with water.

Stop Use

Stop use if rash/itching occurs; consult doctor

Ask Doctor

Stop use if rash/itching occurs; consult doctor

Keep Oot Of Reach Of Children

Keep away from children; if swallowed, get medical help immediately

Directions

Roll on target area; massage gently. Do not cover immediately.

Other information

20º-25℃; no freezing/ direct sunlight

Inactive ingredients

Mineral Oil,Glycerin, Yellow Beeswax, Calendula Officinalis Flower Extract, Arnica Montana Flower Extract, Tocopherol